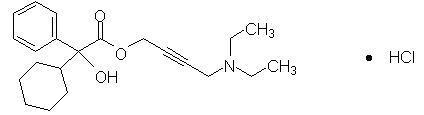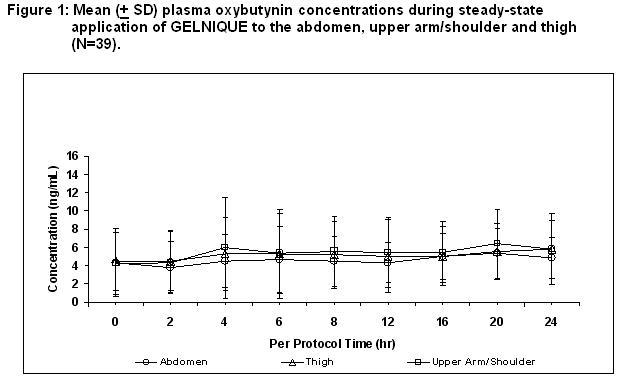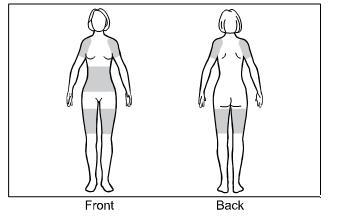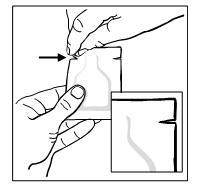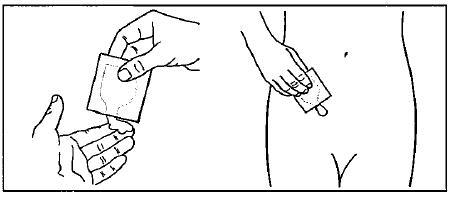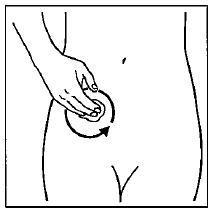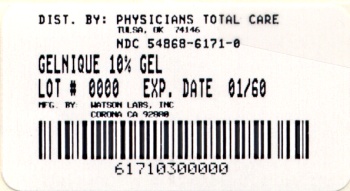 DRUG LABEL: GELNIQUE
NDC: 54868-6171 | Form: GEL
Manufacturer: Physicians Total Care, Inc.
Category: prescription | Type: HUMAN PRESCRIPTION DRUG LABEL
Date: 20090115

ACTIVE INGREDIENTS: OXYBUTYNIN CHLORIDE 100 mg/1 g

HIGHLIGHTS OF PRESCRIBING INFORMATION

These highlights do not include all the information needed to use GELNIQUE safely and effectively.
See full prescribing information for GELNIQUE.
GELNIQUE (oxybutynin chloride) gel for topical use
Initial U.S. Approval: 1975

1 INDICATIONS AND USAGE

GELNIQUE is an antimuscarinic agent indicated for the treatment of overactive bladder with symptoms of urge urinary incontinence, urgency, and frequency. (1)

2 DOSAGE AND ADMINISTRATION

- Apply contents of one sachet of GELNIQUE once daily to dry, intact skin on the abdomen, upper arms/shoulders, or thighs. (2)
- Rotate application sites, avoiding use of the same site on consecutive days. (2)
- GELNIQUE is for topical application only and should not be ingested. (2)

3 DOSAGE FORMS AND STRENGTHS

Sachet: 1 gram unit dose (1.14 mL) 100 mg/g oxybutynin chloride gel. (3)

4 CONTRAINDICATIONS

- Urinary retention (4)
- Gastric retention (4)
- Uncontrolled narrow-angle glaucoma (4)
- Known hypersensitivity to GELNIQUE , including skin hypersensitivity (4)

5 WARNINGS AND PRECAUTIONS

- Urinary Retention: Use caution in patients with clinically significant bladder outflow obstruction because of the risk of urinary retention. (5.1)
- Gastrointestinal Disorders: Use caution in patients with gastrointestinal obstructive disorders or decreased intestinal motility because of the risk of gastric retention. Use caution in patients with gastroesophageal reflux and/or those taking drugs that can cause or exacerbate esophagitis (5.2)
- Skin Hypersensitivity: Discontinue GELNIQUE in patients with skin hypersensitivity. (5.3)
- Skin transference: Advise patients to cover the application site with clothing if skin-to-skin contact at the application site is anticipated. Wash hands immediately after product application. (5.4)
- Flammable Gel: Contains alcohol-based gel. Avoid open fire or smoking until the gel has dried. (5.5)

6 ADVERSE REACTIONS

The most common adverse reactions (incidence > 5% and > placebo) were dry mouth and application site reactions. (6)

To report SUSPECTED ADVERSE REACTIONS, contact Watson Pharmaceuticals, Inc. at 1-800-272-5525 or FDA at 1-800-FDA-1088 or www.fda.gov/medwatch

7 DRUG INTERACTIONS

Other Anticholinergics (antimuscarinics): Concomitant use with other anticholinergic agents may increase the frequency and/or severity of dry mouth, constipation, blurred vision and other anticholinergic pharmacological effects. (7.1)

FULL PRESCRIBING INFORMATION

1 INDICATIONS AND USAGE

GELNIQUE is indicated for the treatment of overactive bladder with symptoms of urge urinary incontinence, urgency, and frequency [see Clinical Studies 14].

2 DOSAGE AND ADMINISTRATION

The contents of one sachet of GELNIQUE should be applied once daily to dry, intact skin on the abdomen, upper arms/shoulders, or thighs. Application sites should be rotated. Application of GELNIQUE should not be made to the same site on consecutive days [see Clinical Pharmacology (12.3)].

GELNIQUE is for topical application only and should not be ingested.

3 DOSAGE FORMS AND STRENGTHS

Each sachet contains a 1 gram unit dose (1.14 mL) of 100 mg/g oxybutynin chloride gel.

4 CONTRAINDICATIONS

The use of GELNIQUE is contraindicated in the following conditions:

- Urinary retention
- Gastric retention
- Uncontrolled narrow-angle glaucoma
- Known hypersensitivity to GELNIQUE, including skin hypersensitivity [see Warnings and Precautions (5.3)].

5 WARNINGS AND PRECAUTIONS

5.1 Urinary Retention

Administer GELNIQUE with caution in patients with clinically significant bladder outflow obstruction because of the risk of urinary retention.

5.2 Use in Patients with Gastrointestinal Disorders

Administer GELNIQUE with caution to patients with gastrointestinal obstructive disorders because of the risk of gastric retention.

GELNIQUE, like other anticholinergic drugs, may decrease gastrointestinal motility and should be used with caution in patients with conditions such as ulcerative colitis or intestinal atony. GELNIQUE should be used with caution in patients who have gastroesophageal reflux and/or who are concurrently taking drugs (such as bisphosphonates) that can cause or exacerbate esophagitis.

5.3 Skin Hypersensitivity

In a controlled clinical trial of skin sensitization, 1 of 200 patients (0.5%) demonstrated skin hypersensitivity to GELNIQUE. Patients who develop skin hypersensitivity to GELNIQUE should discontinue drug treatment.

5.4 Skin Transference

Transfer of oxybutynin to another person can occur when vigorous skin-to-skin contact is made with the application site. To minimize the potential transfer of oxybutynin from GELNIQUE-treated skin to another person, patients should cover the application site with clothing after the gel has dried if direct skin-to-skin contact at the application site is anticipated [see Clinical Pharmacology (12.3)]. Patients should wash their hands immediately after application of GELNIQUE.

5.5 Flammable Gel

GELNIQUE is an alcohol-based gel and is therefore flammable. Avoid open fire or smoking until gel has dried.

5.6 Myasthenia Gravis

Administer GELNIQUE with caution in patients with myasthenia gravis, a disease characterized by decreased cholinergic activity at the neuromuscular junction.

6 ADVERSE REACTIONS

Because clinical trials are conducted under widely varying conditions, adverse reaction rates observed in the clinical trials of a drug cannot be directly compared to rates in the clinical trial of another drug and may not reflect the rates observed in practice.

6.1 Clinical Studies Experience

The safety of GELNIQUE was evaluated in 789 patients (389 randomized to GELNIQUE 1 g and 400 randomized to placebo) during a randomized, placebo-controlled, double-blind, 12-week clinical efficacy and safety study. A subset of these 789 patients (N=216) participated in the 14-week open-label safety extension that followed the placebo-controlled study. Of 216 patients in the safety extension, 107 were randomized to placebo gel during the double-blind, placebo-controlled 12-week study. In the combined double-blind, placebo-controlled study and the open-label safety extension, a total of 496 patients were exposed to at least one dose of GELNIQUE. Four hundred thirty-one (431) patients received at least 12 weeks of GELNIQUE treatment and 85 patients received 26 weeks of GELNIQUE treatment. The study population primarily consisted of Caucasian women (approximately 90%) with an average age of 59 years who had overactive bladder with urge urinary incontinence.

Table 1 lists adverse events, regardless of causality, that were reported in the randomized, double-blind, placebo-controlled 12-week study at an incidence greater than placebo and in greater than 2% of patients treated with GELNIQUE.

Table 1: Common Adverse Events in the Randomized, Double-blind, Placebo-controlled 12-Week Study (>2% and > placebo)
Adverse Event | GELNIQUE 1 gram N=389 n (%) | Placebo N=400 n (%)
Dry mouth | 29 (7.5) | 11 (2.8)
Urinary tract infection | 27 (6.9) | 17 (4.3)
Application site reactions* | 21 (5.4) | 4 (1.0)
Upper respiratory tract infection | 21 (5.4) | 20 (5.0)
Dizziness | 11 (2.8) | 4 (1.0)
Nasopharyngitis | 11 (2.8) | 9 (2.3)
Fatigue | 8 (2.1) | 4 (1.0)
Gastroenteritis viral | 8 (2.1) | 7 (1.8)
* Includes application site pruritus, dermatitis, papules, anesthesia, erythema, irritation, pain and papules

The most common adverse reactions, defined as adverse events judged by the investigator to be reasonably associated with the use of study drug, that were reported in ≥ 1% of GELNIQUE-treated patients were dry mouth (6.9%), application site reactions (5.4%), dizziness (1.5%), headache (1.5%), constipation (1.3%), and pruritus (1.3%). Application site pruritus (2.1%) and application site dermatitis (1.8%) were the most commonly reported application site reactions. A majority of treatment-related adverse events were described as mild or moderate in intensity, except for two patients reporting severe headache.

No serious adverse events were judged by the investigator to be treatment-related during the randomized, double-blind, placebo-controlled 12-week study. The most common adverse reaction leading to drug discontinuation was application site reaction (0.8% with GELNIQUE versus 0.3% with placebo).

The most common adverse reactions reported during the 14-week open-label extension study were application site reactions (6.0%) and dry mouth (1.9%). The most common reason for premature discontinuation was application site reactions (9 patients or 4.2%). Two of these 9 patients experienced application site reactions of severe intensity (dermatitis, urticaria, and erythema).

7 DRUG INTERACTIONS

No specific drug-drug interaction studies have been performed with GELNIQUE.

7.1 Other Anticholinergics

The concomitant use of GELNIQUE with other anticholinergic (antimuscarinic) agents may increase the frequency and/or severity of dry mouth, constipation, blurred vision, somnolence and other anticholinergic pharmacological effects.

8 USE IN SPECIFIC POPULATIONS

8.1 Pregnancy

Pregnancy Category B

There are no adequate and well-controlled studies of topical or oral oxybutynin use in pregnant women. Subcutaneous administration to rats at doses up to 25 mg/kg (approximately 50 times the human exposure based on surface area) and to rabbits at doses up to 0.4 mg/kg (approximately 1 times the human exposure) revealed no evidence of harm to the fetus due to oxybutynin chloride. The safety of GELNIQUE administration to women who are or who may become pregnant has not been established. Therefore, GELNIQUE should not be given to pregnant women unless, in the judgment of the physician, the probable clinical benefits outweigh the possible hazards.

8.3 Nursing Mothers

It is not known whether oxybutynin is excreted in human milk. Because many drugs are excreted in human milk, caution should be exercised when GELNIQUE is administered to a nursing woman.

8.4 Pediatric Use

Safety and effectiveness of GELNIQUE in pediatric patients have not been established.

8.5 Geriatric Use

Of the 496 patients exposed to GELNIQUE in the randomized, double-blind, placebo-controlled 12-week study and the 14-week safety extension study, 188 patients (38%) were 65 years of age and older. No overall differences in safety or effectiveness were observed between these patients and younger patients.

8.6 Renal Impairment

There is no experience with the use of GELNIQUE in patients with renal impairment.

8.7 Hepatic Impairment

There is no experience with the use of GELNIQUE in patients with hepatic impairment.

10 OVERDOSAGE

Overdosage with oxybutynin has been associated with anticholinergic effects including central nervous system excitation, flushing, fever, dehydration, cardiac arrhythmia, vomiting, and urinary retention. Oral ingestion of 100 mg oxybutynin chloride in association with alcohol has been reported in a 13-year-old boy who experienced memory loss, and in a 34-year-old woman who developed stupor, followed by disorientation and agitation on awakening, dilated pupils, dry skin, cardiac arrhythmia, and retention of urine. Both patients recovered fully with symptomatic treatment.

Plasma concentrations of oxybutynin begin to decline 24 hours after GELNIQUE application. If overexposure occurs, monitor patients until symptoms resolve.

11 DESCRIPTION

Oxybutynin is an antispasmodic, antimuscarinic agent. GELNIQUE (oxybutynin chloride) is a clear and colorless hydroalcoholic gel containing 100 mg oxybutynin chloride per gram of gel. GELNIQUE is available in a 1 gram (1.14 mL) unit dose that contains 100 mg oxybutynin chloride. Oxybutynin is delivered as a racemate of R- and S- isomers. Chemically, oxybutynin chloride is d, l (racemic) 4-(Diethylamino)-2-butynyl (±)-α-phenylcyclohexaneglycolate hydrochloride.

The empirical formula of oxybutynin is C22H31NO3•HCl. Its structural formula is:

Oxybutynin chloride is a white powder with a molecular weight of 393.95.

Inactive ingredients in GELNIQUE are alcohol, USP; glycerin, USP; hydroxypropyl cellulose, NF; sodium hydroxide, NF; and purified water, USP.

12 CLINICAL PHARMACOLOGY

12.1 Mechanism of Action

Oxybutynin acts as a competitive antagonist of acetylcholine at postganglionic muscarinic receptors, resulting in relaxation of bladder smooth muscle. In patients with conditions characterized by involuntary detrusor contractions, cystometric studies have demonstrated that oxybutynin increases maximum urinary bladder capacity and increases the volume to first detrusor contraction.

Oxybutynin is a racemic (50:50) mixture of R- and S- isomers. Antimuscarinic activity resides predominantly with the R-isomer. The active metabolite, N-desethyloxybutynin, has pharmacological activity on the human detrusor muscle that is similar to that of oxybutynin in in vitro studies.

12.3 Pharmacokinetics

Absorption

Oxybutynin is transported across intact skin and into the systemic circulation by passive diffusion across the stratum corneum. Steady-state concentrations are achieved within 7 days of continuous dosing. Absorption of oxybutynin is similar when GELNIQUE is applied to the abdomen, upper arm/shoulders or thighs. Mean plasma concentrations during a randomized, crossover study of the three recommended application sites in 39 healthy men and women are shown in Figure 1.

Average steady-state plasma oxybutynin concentrations were 4.7, 5.2, and 5.5 ng/mL for the abdomen, upper arm/shoulder and thigh application sites, respectively (Table 2).

Table 2: Mean (SD) steady-state pharmacokinetic parameters for oxybutynin following GELNIQUE application to the abdomen, upper arm/shoulder and thigh (N=39).
Application Site | AUC 0-24 (ng•hr/mL) | Cmax (ng/mL) | Cavg (ng/mL)
Abdomen | 112.7 (58.00) | 6.8 (3.93) | 4.7 (2.39)
Upper Arm/Shoulder | 133.8 (81.58) | 8.3 (5.97) | 5.5 (3.37)
Thigh | 125.1 (84.67) | 7.0 (4.95) | 5.2 (3.50)

Distribution

Oxybutynin is widely distributed in body tissues following systemic absorption. The volume of distribution was estimated to be 193 L after intravenous administration of 5 mg oxybutynin chloride.

Metabolism

Oxybutynin is metabolized primarily by the cytochrome P450 enzyme systems, particularly CYP3A4, found mostly in the liver and gut wall. Metabolites include phenylcyclohexylglycolic acid, which is pharmacologically inactive, and N-desethyloxybutynin (DEO), which is pharmacologically active.

Transdermal administration of oxybutynin bypasses the first-pass gastrointestinal and hepatic metabolism, reducing the formation of the N-desethyloxybutynin metabolite. Only small amounts of CYP3A4 are found in skin, limiting pre-systemic metabolism during transdermal absorption. The AUC ratio of N-desethyloxybutynin metabolite to parent compound following multiple transdermal applications is approximately 1:1 for GELNIQUE.

Following intravenous administration, the elimination half-life of oxybutynin is approximately 2 hours. After the final steady-state dose of GELNIQUE, oxybutynin and N-desethyloxybutynin demonstrated biphasic elimination with plasma concentrations beginning to decrease 24 hours after dosing. Elimination was more rapid between 24 and 48 hours after dosing, during which time plasma concentrations of oxybutynin and N-desethyloxybutynin declined by about one-half. This rapid elimination phase was followed by a more prolonged terminal elimination phase. The apparent elimination half-lives including the terminal elimination phase were 64 hours and 82 hours for oxybutynin and DEO, respectively.

Excretion

Oxybutynin is extensively metabolized by the liver, with less than 0.1% of the administered dose excreted unchanged in the urine. Less than 0.1% of the administered dose is excreted as the metabolite N-desethyloxybutynin.

Person-to-Person Transference

The potential for dermal transfer of oxybutynin from a treated person to an untreated person was evaluated in a single-dose study where subjects dosed with GELNIQUE engaged in vigorous contact with an untreated partner for 15 minutes, either with (N=14 couples) or without (N=12 couples) clothing covering the application area. The untreated partners not protected by clothing demonstrated detectable plasma concentrations of oxybutynin (mean Cmax = 0.94 ng/mL). Two of the 14 untreated subjects participating in the clothing-to-skin contact regimen had measurable oxybutynin plasma concentrations (Cmax ≤ 0.1 ng/mL) during the 48 hours following contact with treated subjects; oxybutynin was not detectable with the remaining 12 untreated subjects.

Use of Sunscreen

The effect of sunscreen on the absorption of oxybutynin when applied 30 minutes before or 30 minutes after GELNIQUE application was evaluated in a single-dose randomized crossover study (N=16). Concomitant application of sunscreen, either before or after GELNIQUE application, had no effect on the systemic exposure of oxybutynin.

Showering

The effect of showering on the absorption of oxybutynin was evaluated in a randomized, steady-state crossover study under conditions of no shower, or showering 1, 2 or 6 hours after GELNIQUE application (N=20). The results of the study indicate that showering after one hour does not affect the overall systemic exposure to oxybutynin.

Race

The effect of race on the pharmacokinetics of GELNIQUE has not been studied.

Geriatric Patients

Available data suggest that there are no significant differences in the pharmacokinetics of oxybutynin based on geriatric status in patients following administration of GELNIQUE [see Use in Specific Populations (8.5)].

Pediatric Patients

The pharmacokinetics of oxybutynin and N-desethyloxybutynin have not been evaluated in individuals younger than 18 years of age [see Use in Specific Populations (8.4)].

Gender

Available data suggest that there are no significant differences in the pharmacokinetics of oxybutynin based on gender in healthy volunteers following administration of GELNIQUE.

Renal Impairment

There is no experience with the use of GELNIQUE in patients with renal insufficiency.

Hepatic Impairment

There is no experience with the use of GELNIQUE in patients with hepatic insufficiency.

13 NONCLINICAL TOXICOLOGY

13.1 Carcinogenesis, Mutagenesis, Impairment of Fertility

A 24-month study in rats at dosages of oxybutynin chloride of 20, 80 and 160 mg/kg showed no evidence of carcinogenicity. These doses are approximately 6, 25 and 50 times the maximum exposure in humans taking an oral dose, based on body surface area. Oxybutynin chloride showed no increase of mutagenic activity when tested in Schizosaccharomyces pompholiciformis, Saccharomyces cerevisiae, and Salmonella typhimurium test systems. Reproduction studies with oxybutynin chloride in the mouse, rat, hamster, and rabbit showed no definite evidence of impaired fertility.

14 CLINICAL STUDIES

The efficacy and safety of GELNIQUE were evaluated in a single randomized, double-blind, placebo-controlled, parallel group 12-week study for the treatment of overactive bladder with symptoms of urge incontinence, urgency and frequency. Key entry criteria included adults with symptomatic overactive bladder with an average of ≥ 4 incontinence episodes in a 3-day period and at least 8 micturitions per day. Patients were randomized to daily applications of GELNIQUE 1 gram or matching placebo gel. A total of 389 patients received GELNIQUE and 400 patients received placebo gel. The majority of patients were Caucasian (86.3%) and female (89.2%), with a mean age of 59.4 years (range: 18 to 88 years). The average duration of urinary incontinence was approximately 8.5 years and approximately 75% of patients had no prior pharmacological treatment for urinary incontinence.

Patients treated with GELNIQUE experienced a statistically significant decrease in the number of urinary incontinence episodes per day from baseline to endpoint (the primary efficacy endpoint) compared with placebo (p<0.0001) as well as a decrease in the average daily urinary frequency (p=0.0017) and an increase in the average urine volume per void (p=0.0018).

Mean and median change from baseline in daily incontinence episodes (primary endpoint), urinary frequency, and urinary void volume (secondary endpoints) between placebo and GELNIQUE are summarized in Table 3.

Table 3: Mean and median change from baseline for incontinence episodes, urinary frequency, and urinary void volume at Week 12 (LOCF*).
Parameter | GELNIQUE 1 gram (N=389) |  | Placebo (N=400)
Parameter | Mean (SD) | Median | Mean (SD) | Median
Daily Incontinence Episodes
Baseline | 5.4 (3.26) | 4.7 | 5.4 (3.28) | 4.7
Change from baseline | -3.0 (2.73) | -2.7 | -2.5 (3.06) | -2.0
Mean difference [GELNIQUE – placebo] (95% CI) | -0.5 (-0.14, -0.87)
P-value vs. placebo | <0.0001
Daily Urinary Frequency
Baseline | 12.4 (3.34) | 11.7 | 12.2 (3.32) | 11.3
Change from baseline | -2.7 (3.21) | -2.7 | -2.0 (2.82) | -1.7
P-value vs. placebo | 0.0017
Urinary Void Volume (mL)
Baseline | 163.4 (65.85) | 160.1 | 167.9 (68.40) | 160.6
Change from Baseline | 21.0 (65.33) | 11.5 | 3.8 (53.79) | 0.0
P-value vs. placebo | 0.0018
*Last-Observation-Carried-Forward statistical imputation for missing data

16 HOW SUPPLIED/STORAGE AND HANDLING

Unit Dose: Heat-sealed sachet containing 1 gram (1.14 mL) of GELNIQUE gel for topical use.

Carton of 30 Sachets NDC 54868-6171-0

Storage

Store at 25°C (77°F); excursions permitted to 15-30°C (59-86°F). See USP controlled room temperature. Protect from moisture and humidity. Apply immediately after the sachets are opened and contents expelled. Discard used sachets in household trash in a manner that prevents accidental application or ingestion by children, pets, or others.

Keep out of reach of children.

17 PATIENT COUNSELING INFORMATION

[see FDA-approved Patient Labeling]

17.1 Instructions for Use

GELNIQUE is for topical application only and should not be ingested.

GELNIQUE should not be applied to recently shaved skin surfaces. Patients should wash hands immediately after product application. Application sites should not be subject to showering or water immersion for 1 hour after product application. Application sites should be covered with clothing if close skin-to-skin contact at the application site is anticipated.

Alcohol based gels are flammable. Avoid open fire or smoking until the gel has dried.

17.2 Important Anticholinergic Adverse Reactions

Patients should be informed that anticholinergic (antimuscarinic) agents, such as GELNIQUE, may produce clinically significant adverse reactions related to anticholinergic pharmacological activity including constipation, urinary retention and blurred vision. Heat prostration (due to decreased sweating) can occur when anticholinergics such as GELNIQUE are used in a hot environment. Because anticholinergic (antimuscarinic) agents, such as GELNIQUE, may produce dizziness or blurred vision, patients should be advised to exercise caution in decisions to engage in potentially dangerous activities until GELNIQUE’s effects have been determined. Patients should be informed that alcohol may enhance the drowsiness caused by anticholinergic (antimuscarinic) agents such as GELNIQUE.

FDA-Approved Patient Labeling

Information for the Patient

GELNIQUE
(oxybutynin chloride) 10% gel

(For Topical Use Only)

Read this information carefully before you begin treatment. Read the information whenever you refill a prescription as there may be something new. This information does not take the place of talking with your doctor about your medical condition or your treatment. If you have any questions about GELNIQUE, ask your doctor. Only your doctor can determine if GELNIQUE is right for you.

What is GELNIQUE?

GELNIQUE is a clear and colorless topical gel approved for the treatment of overactive bladder with symptoms of urge urinary incontinence, urgency, and frequency. It delivers the active ingredient, oxybutynin, directly into your bloodstream through your skin.

Overactive bladder makes it hard to control urination (passing water). Overactive bladder can make you urinate more often (increased frequency) or make you feel the need to urinate suddenly (urgency). Overactive bladder can also lead to accidental urine loss (leaking or wetting oneself).

The active ingredient in GELNIQUE, oxybutynin, is formulated into a topical gel for daily application. GELNIQUE delivers the medicine slowly and constantly through your skin and into your bloodstream for 24 hours. GELNIQUE contains the same active ingredient as oxybutynin tablets, patches and syrup.

Who should not use GELNIQUE?

Do not use GELNIQUE if you have the following medical conditions:

- Urinary retention. Your bladder does not empty or does not empty completely when you urinate.
- Gastric retention. Your stomach empties slowly or incompletely after a meal.
- Uncontrolled narrow-angle glaucoma (high pressure in your eye). Tell your doctor if you have glaucoma or a family history of glaucoma.
- Allergy to oxybutynin or the inactive ingredients in GELNIQUE. If you need to know the inactive ingredients, ask your doctor or pharmacist. If you have allergies to topical medical products, tell your doctor.

If you have certain other medical conditions, use GELNIQUE with caution. Tell your doctor about all your medical conditions, especially if you have any of the following:

- Pregnancy or breastfeeding
- Liver disease
- Kidney disease
- Difficulty in emptying bladder completely
- Constipation or difficulty in emptying bowels
- Ulcerative colitis (inflamed bowels)
- Gastric reflux disease or esophagitis (inflamed esophagus, the tube between your mouth and stomach)

Tell your doctor about all the medicines you take, including prescription and non-prescription medicines and supplements. Some of them may cause problems if you administer GELNIQUE. Also, GELNIQUE may affect how some medicines are absorbed from the stomach.

What should I avoid while using GELNIQUE?

Do not apply GELNIQUE to areas of the skin that have been treated with oils, lotions, or powders as that could affect the amount of oxybutynin absorbed through the skin. However, GELNIQUE may be used with sunscreen.

GELNIQUE is a gel which contains alcohol. Gels with alcohol are flammable. Avoid fire, flame or smoking until the gel has dried.

What are the possible side effects of GELNIQUE?

You may have skin changes at the site of application, such as itching, rash, or redness. If uncomfortable irritation or excessive itchiness continues, tell your doctor.

Oxybutynin may cause sleepiness or blurred vision, so be careful when driving or operating machinery. Drinking alcoholic beverages may increase these effects.

Since oxybutynin treatment may decrease sweating, you may overheat or have fever or heat stroke if you are in warm or hot temperatures.

The most common side effect of GELNIQUE is dry mouth. Other possible side effects include application site skin changes (such as itching, rash, or redness), headache, constipation, and dizziness. If you take other medicines that cause dry mouth, constipation, or sleepiness, GELNIQUE can increase those effects.

Tell your doctor if you have any side effect that bothers you or that does not go away. These are not all the possible side effects of GELNIQUE. For more information, ask your doctor or pharmacist.

Call your doctor for medical advice about side effects. You may report side effects to the FDA at 1-800-FDA-1088.

How should I use GELNIQUE?

GELNIQUE is for application to the skin only. GELNIQUE SHOULD NOT BE TAKEN BY MOUTH.

Important: Avoid contact with eyes, nose, open sores, recently shaved skin, and skin with rashes or other areas not approved for the application of GELNIQUE.

1. Step 1. The approved application sites for GELNIQUE are the shaded areas shown in Figure A. These are the abdomen (stomach area), upper arms/shoulder, and thigh.
  Select an approved site for the application of GELNIQUE.
  Changing the approved application sites with each dose is recommended and may help you to find the most comfortable areas for applying GELNIQUE.
  The approved application sites are shown below. Do not apply GELNIQUE in an area that is not approved.
  Figure A:
2. Step 2. Wash your hands with soap and water before applying GELNIQUE.
3. Step 3. Wash the area where GELNIQUE will be applied with mild soap and water.
  Allow the area to dry completely.
4. Step 4. Tear the packet of GELNIQUE open at the indentation just before use. See Figure B.
  Figure B:
  Squeeze the entire contents of the packet into the palm of your hand or squeeze directly onto the application site. See Figure C.
  Squeeze from the bottom of the packet toward the open end. Repeat until the packet is empty. The amount of gel in each packet will be about the size of a nickel on your skin.
  Figure C:
5. Step 5. Gently rub GELNIQUE into your skin until it dries.
  Do not continue rubbing after GELNIQUE has dried. If applying GELNIQUE to the stomach, care should be taken to avoid the area around the navel (belly-button). See Figure D.
  Figure D:
6. Step 6. Carefully throw away the open packet of GELNIQUE so that children and pets are not exposed to it.
7. Step 7. After applying GELNIQUE, immediately wash your hands thoroughly with soap and water.
  Avoid bathing, swimming, showering, exercising or immersing the application site in water for one hour after application.
  The application site may be covered with clothing once GELNIQUE has dried.

What should I do if someone else is exposed to GELNIQUE?

If someone else is exposed to GELNIQUE by direct contact with the gel or at the application site of GELNIQUE, that person should wash the area of contact with soap and water as soon as possible.

What should I do if I get GELNIQUE in my eyes?

If you get GELNIQUE in your eyes, rinse your eyes right away with warm, clean water to flush out any GELNIQUE. Seek medical attention if needed.

General advice about GELNIQUE

Medicines are sometimes prescribed for conditions that are not mentioned in patient information leaflets. Do not give GELNIQUE to other people, even if they have the same symptoms you have. It may harm them.

This leaflet summarizes the most important information about GELNIQUE. If you would like more information, talk with your doctor. You can ask your pharmacist or doctor for information about GELNIQUE that is written for health professionals. You can get more information about GELNIQUE from the product information department at 1-800-272-5525 or by selecting patient information at the GELNIQUE Website located at www.GELNIQUE.com.

Store at room temperature, 25°C (77°F). Temporary storage between 15 - 30°C (59 - 86°F) is also permitted. Keep GELNIQUE and all medications in a safe, secure place and out of the reach of children.

Address medical inquiries to:
Watson Pharma, Inc.
Medical Communications
P. O. Box 1953
Morristown, NJ 07962-1953
800-272-5525

Watson Pharmaceuticals, Inc.
Corona, CA 92880 USA

©2008 Watson Pharmaceuticals, Inc., Corona, CA 92880

Relabeling of "Additional Barcode Label" by:
Physicians Total Care, Inc.
Tulsa, OK 74146

PRINCIPAL DISPLAY PANEL

GELNIQUE

1 gram (1.14 mL)